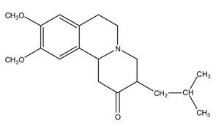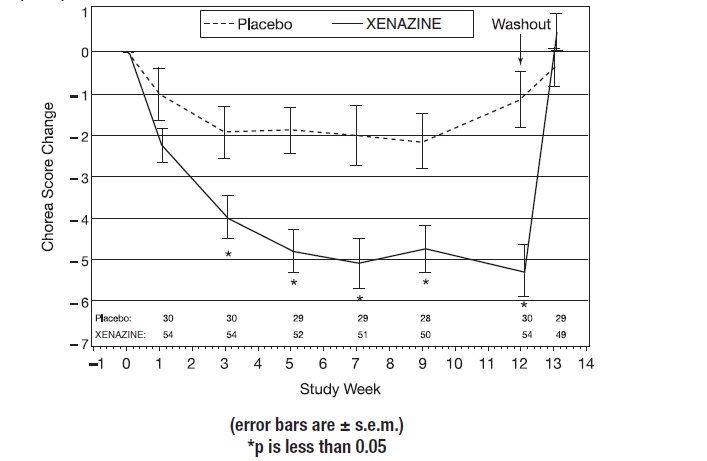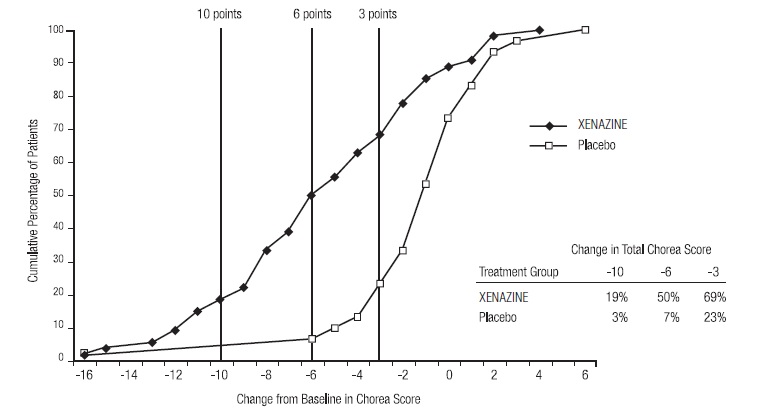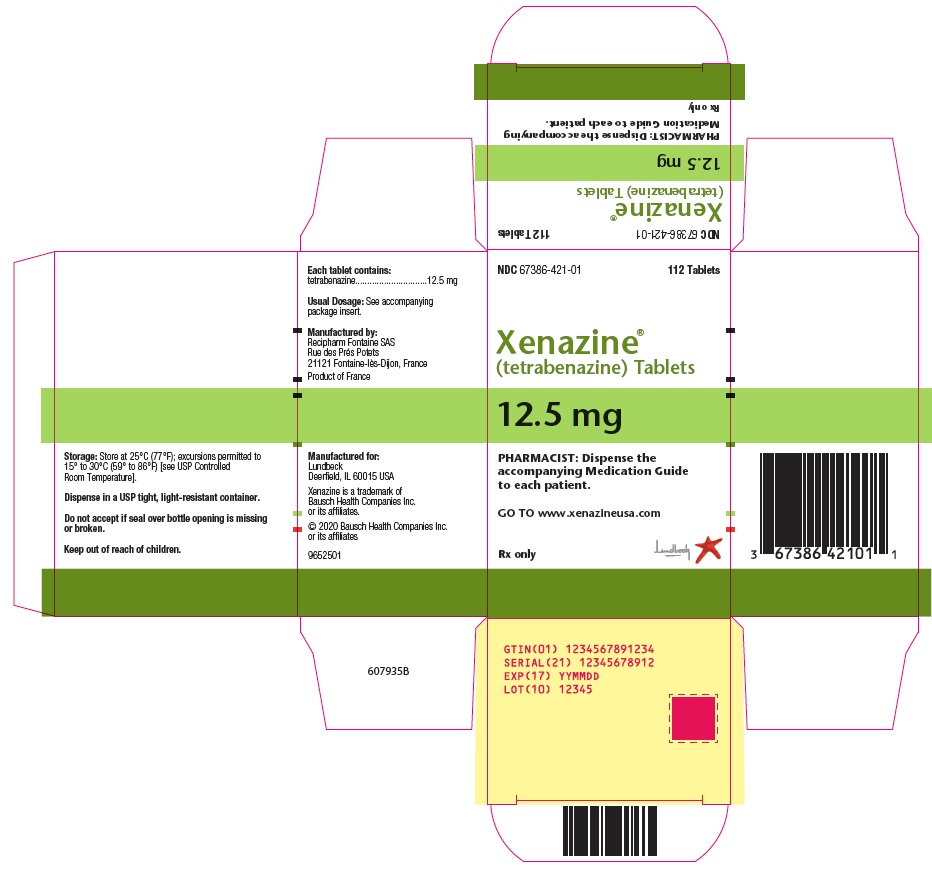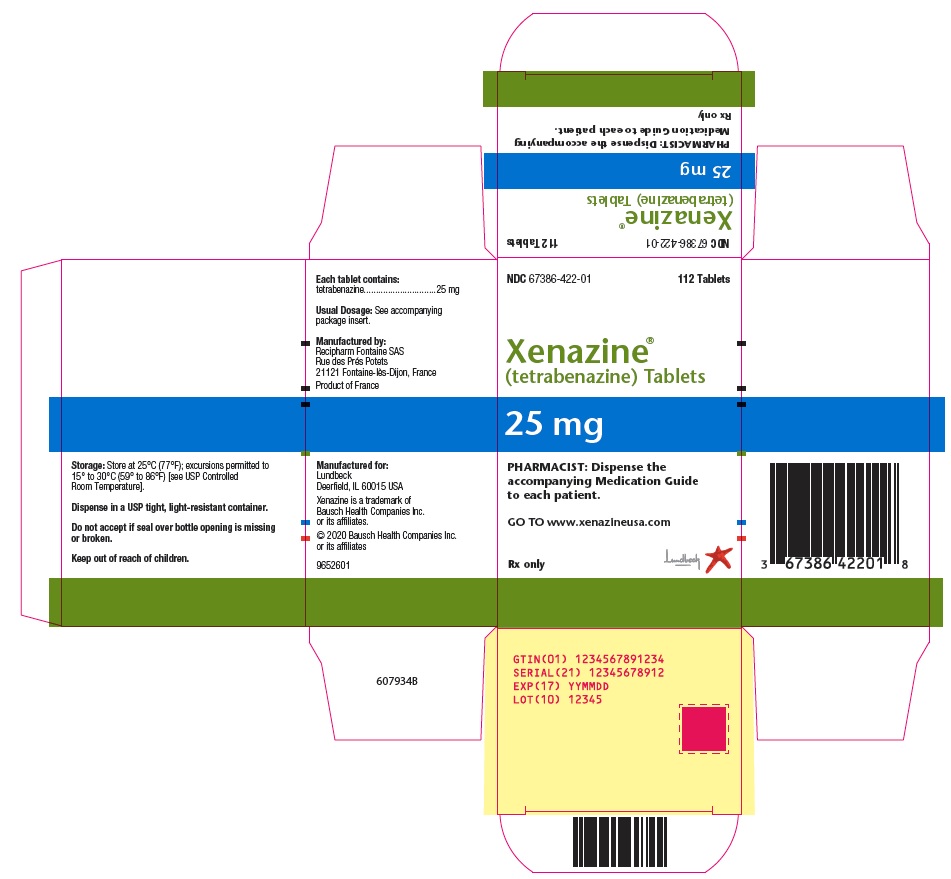 DRUG LABEL: Xenazine
NDC: 67386-421 | Form: TABLET
Manufacturer: Lundbeck Pharmaceuticals LLC
Category: prescription | Type: HUMAN PRESCRIPTION DRUG LABEL
Date: 20191101

ACTIVE INGREDIENTS: TETRABENAZINE 12.5 mg/1 1
INACTIVE INGREDIENTS: LACTOSE, UNSPECIFIED FORM; magnesium stearate; starch, corn; talc

HIGHLIGHTS OF PRESCRIBING INFORMATION

These highlights do not include all the information needed to use XENAZINE safely and effectively. See full prescribing information for XENAZINE.
XENAZINE® (tetrabenazine) tablets, for oral use
Initial U.S. Approval: 2008

WARNING: DEPRESSION AND SUICIDALITY

See full prescribing information for complete boxed warning.

- Increases the risk of depression and suicidal thoughts and behavior (suicidality) in patients with Huntington's disease (5.1)
- Balance risks of depression and suicidality with the clinical need for control of chorea when considering the use of XENAZINE (5.2)
- Monitor patients for the emergence or worsening of depression, suicidality, or unusual changes in behavior (5.1)
- Inform patients, caregivers and families of the risk of depression and suicidality and instruct to report behaviors of concern promptly to the treating physician (5.1)
- Exercise caution when treating patients with a history of depression or prior suicide attempts or ideation (5.1)
- XENAZINE is contraindicated in patients who are actively suicidal, and in patients with untreated or inadequately treated depression (4, 5.1)

1 INDICATIONS AND USAGE

XENAZINE is a vesicular monoamine transporter 2 (VMAT) inhibitor indicated for the treatment of chorea associated with Huntington’s disease. (1)

2 DOSAGE AND ADMINISTRATION

- Individualization of dose with careful weekly titration is required. The 1st week’s starting dose is 12.5 mg daily; 2nd week, 25 mg (12.5 mg twice daily); then slowly titrate at weekly intervals by 12.5 mg to a tolerated dose that reduces chorea. (2.1, 2.2)
- Doses of 37.5 mg and up to 50 mg/day should be administered in three divided doses per day with a maximum recommended single dose not to exceed 25 mg. (2.2)
- Patients requiring doses above 50 mg/day should be genotyped for the drug metabolizing enzyme CYP2D6 to determine if the patient is a poor metabolizer (PM) or an extensive metabolizer (EM). (2.2, 5.3)
- Maximum daily dose in PMs: 50 mg with a maximum single dose of 25 mg (2.2)
- Maximum daily dose in EMs and intermediate metabolizers (IMs): 100 mg with a maximum single dose of 37.5 mg (2.2)
- If serious adverse reactions occur, titration should be stopped and the dose should be reduced. If the adverse reaction(s) do not resolve, consider withdrawal of XENAZINE. (2.2)

3 DOSAGE FORMS AND STRENGTHS

Tablets: 12.5 mg non-scored and 25 mg scored (3)

4 CONTRAINDICATIONS

- Actively suicidal, or who have depression which is untreated or undertreated (4, 5.1)
- Hepatic impairment (4, 8.6, 12.3)
- Taking monoamine oxidase inhibitors (MAOIs) or reserpine (4, 7.2, 7.3)
- Taking deutetrabenazine or valbenazine (4, 7.7)

5 WARNINGS AND PRECAUTIONS

- Periodically reevaluate the benefit and potential for adverse effects such as worsening mood, cognition, rigidity, and functional capacity. (5.2)
- Do not exceed 50 mg/day and the maximum single dose should not exceed 25 mg if administered in conjunction with a strong CYP2D6 inhibitor (e.g., fluoxetine, paroxetine). (5.3, 7.1)
- Neuroleptic Malignant Syndrome (NMS): Discontinue if this occurs. (5.4, 7.6)
- Restlessness, agitation, akathisia and parkinsonism: Reduce dose or discontinue if occurs. (5.5, 5.6)
- Sedation/Somnolence: May impair patient’s ability to drive or operate complex machinery (5.7)
- QTc prolongation: Not recommended in combination with other drugs that prolong QTc (5.8)

6 ADVERSE REACTIONS

Most common adverse reactions (greater than 10% and at least 5% greater than placebo) were: sedation/somnolence, fatigue, insomnia, depression, akathisia, anxiety/anxiety aggravated, nausea. (6.1)

To report SUSPECTED ADVERSE REACTIONS, contact Lundbeck’s XENAZINE Information Center at 1-888-882-6013 or FDA at 1-800-FDA-1088 or www.fda.gov/medwatch.

8 USE IN SPECIFIC POPULATIONS

Pregnancy: Based on animal data, may cause fetal harm. (8.1)

FULL PRESCRIBING INFORMATION

WARNING: DEPRESSION AND SUICIDALITY

XENAZINE can increase the risk of depression and suicidal thoughts and behavior (suicidality) in patients with Huntington's disease. Anyone considering the use of XENAZINE must balance the risks of depression and suicidality with the clinical need for control of chorea. Close observation of patients for the emergence or worsening of depression, suicidality, or unusual changes in behavior should accompany therapy. Patients, their caregivers, and families should be informed of the risk of depression and suicidality and should be instructed to report behaviors of concern promptly to the treating physician.

Particular caution should be exercised in treating patients with a history of depression or prior suicide attempts or ideation, which are increased in frequency in Huntington's disease. XENAZINE is contraindicated in patients who are actively suicidal, and in patients with untreated or inadequately treated depression [see Contraindications (4), Warnings and Precautions (5.1)].

1 INDICATIONS AND USAGE

XENAZINE is indicated for the treatment of chorea associated with Huntington’s disease.

2 DOSAGE AND ADMINISTRATION

2.1 General Dosing Considerations

The chronic daily dose of XENAZINE used to treat chorea associated with Huntington’s disease (HD) is determined individually for each patient. When first prescribed, XENAZINE therapy should be titrated slowly over several weeks to identify a dose of XENAZINE that reduces chorea and is tolerated. XENAZINE can be administered without regard to food [see Clinical Pharmacology (12.3)].

2.2 Individualization of Dose

The dose of XENAZINE should be individualized.

Dosing Recommendations Up to 50 mg/day

The starting dose should be 12.5 mg/day given once in the morning. After 1 week, the dose should be increased to 25 mg/day given as 12.5 mg twice a day. XENAZINE should be titrated up slowly at weekly intervals by 12.5 mg daily, to allow the identification of a tolerated dose that reduces chorea. If a dose of 37.5 to 50 mg/day is needed, it should be given in a three times a day regimen. The maximum recommended single dose is 25 mg. If adverse reactions such as akathisia, restlessness, parkinsonism, depression, insomnia, anxiety or sedation occur, titration should be stopped and the dose should be reduced. If the adverse reaction does not resolve, consideration should be given to withdrawing XENAZINE treatment or initiating other specific treatment (e.g., antidepressants) [see Adverse Reactions (6.1)].

Dosing Recommendations Above 50 mg/day

Patients who require doses of XENAZINE greater than 50 mg/day should be first tested and genotyped to determine if they are poor metabolizers (PMs) or extensive metabolizers (EMs) by their ability to express the drug metabolizing enzyme, CYP2D6. The dose of XENAZINE should then be individualized accordingly to their status as PMs or EMs [see Warnings and Precautions (5.3), Use in Specific Populations (8.7), Clinical Pharmacology (12.3)].

Extensive and Intermediate CYP2D6 Metabolizers

Genotyped patients who are identified as extensive (EMs) or intermediate metabolizers (IMs) of CYP2D6, who need doses of XENAZINE above 50 mg/day, should be titrated up slowly at weekly intervals by 12.5 mg daily, to allow the identification of a tolerated dose that reduces chorea. Doses above 50 mg/day should be given in a three times a day regimen. The maximum recommended daily dose is 100 mg and the maximum recommended single dose is 37.5 mg. If adverse reactions such as akathisia, parkinsonism, depression, insomnia, anxiety or sedation occur, titration should be stopped and the dose should be reduced. If the adverse reaction does not resolve, consideration should be given to withdrawing XENAZINE treatment or initiating other specific treatment (e.g., antidepressants) [see Warnings and Precautions (5.3), Use in Specific Populations (8.7), Clinical Pharmacology (12.3)].

Poor CYP2D6 Metabolizers

In PMs, the initial dose and titration is similar to EMs except that the recommended maximum single dose is 25 mg, and the recommended daily dose should not exceed a maximum of 50 mg [see Use in Specific Populations (8.7), Clinical Pharmacology (12.3)].

2.3 Dosage Adjustment with CYP2D6 Inhibitors

Strong CYP2D6 Inhibitors

Medications that are strong CYP2D6 inhibitors such as quinidine or antidepressants (e.g., fluoxetine, paroxetine) significantly increase the exposure to α-HTBZ and β-HTBZ; therefore, the total dose of XENAZINE should not exceed a maximum of 50 mg and the maximum single dose should not exceed 25 mg [see Warnings and Precautions (5.3), Drug Interactions (7.1), Use in Specific Populations (8.7), Clinical Pharmacology (12.3)].

2.4 Discontinuation of Treatment

Treatment with XENAZINE can be discontinued without tapering. Re-emergence of chorea may occur within 12 to 18 hours after the last dose of XENAZINE [see Drug Abuse and Dependence (9.2)].

2.5 Resumption of Treatment

Following treatment interruption of greater than 5 days, XENAZINE therapy should be re-titrated when resumed. For short-term treatment interruption of less than 5 days, treatment can be resumed at the previous maintenance dose without titration.

3 DOSAGE FORMS AND STRENGTHS

XENAZINE tablets are available in the following strengths and packages:

The 12.5 mg XENAZINE tablets are white, cylindrical, biplanar tablets with beveled edges, non-scored, embossed on one side with “CL” and “12.5.”

The 25 mg XENAZINE tablets are yellowish-buff, cylindrical, biplanar tablets with beveled edges, scored, embossed on one side with “CL” and “25.”

4 CONTRAINDICATIONS

XENAZINE is contraindicated in patients:

- Who are actively suicidal, or in patients with untreated or inadequately treated depression [see Warnings and Precautions (5.1)].
- With hepatic impairment [see Use in Specific Populations (8.6), Clinical Pharmacology (12.3)].
- Taking monoamine oxidase inhibitors (MAOIs). XENAZINE should not be used in combination with an MAOI, or within a minimum of 14 days of discontinuing therapy with an MAOI [see Drug Interactions (7.3)].
- Taking reserpine. At least 20 days should elapse after stopping reserpine before starting XENAZINE [see Drug Interactions (7.2)].
- Taking deutetrabenazine or valbenazine [see Drug Interactions (7.7)].

5 WARNINGS AND PRECAUTIONS

5.1 Depression and Suicidality

Patients with Huntington’s disease are at increased risk for depression, suicidal ideation or behaviors (suicidality). XENAZINE increases the risk for suicidality in patients with HD.

In a 12-week, double-blind, placebo-controlled study in patients with chorea associated with Huntington’s disease, 10 of 54 patients (19%) treated with XENAZINE were reported to have an adverse event of depression or worsening depression compared to none of the 30 placebo-treated patients. In two open-label studies (in one study, 29 patients received XENAZINE for up to 48 weeks; in the second study, 75 patients received XENAZINE for up to 80 weeks), the rate of depression/worsening depression was 35%.

In all of the HD chorea studies of XENAZINE (n=187), one patient committed suicide, one attempted suicide, and six had suicidal ideation.

When considering the use of XENAZINE, the risk of suicidality should be balanced against the need for treatment of chorea. All patients treated with XENAZINE should be observed for new or worsening depression or suicidality. If depression or suicidality does not resolve, consider discontinuing treatment with XENAZINE.

Patients, their caregivers, and families should be informed of the risks of depression, worsening depression, and suicidality associated with XENAZINE, and should be instructed to report behaviors of concern promptly to the treating physician. Patients with HD who express suicidal ideation should be evaluated immediately.

5.2 Clinical Worsening and Adverse Effects

Huntington’s disease is a progressive disorder characterized by changes in mood, cognition, chorea, rigidity, and functional capacity over time. In a 12-week controlled trial, XENAZINE was also shown to cause slight worsening in mood, cognition, rigidity, and functional capacity. Whether these effects persist, resolve, or worsen with continued treatment is unknown.

Prescribers should periodically re-evaluate the need for XENAZINE in their patients by assessing the effect on chorea and possible adverse effects, including depression and suicidality, cognitive decline, parkinsonism, dysphagia, sedation/somnolence, akathisia, restlessness, and disability. It may be difficult to distinguish between adverse reactions and progression of the underlying disease; decreasing the dose or stopping the drug may help the clinician distinguish between the two possibilities. In some patients, underlying chorea itself may improve over time, decreasing the need for XENAZINE.

5.3 Laboratory Tests

Before prescribing a daily dose of XENAZINE that is greater than 50 mg/day, patients should be genotyped to determine if they express the drug metabolizing enzyme, CYP2D6. CYP2D6 testing is necessary to determine whether patients are poor metabolizers (PMs), extensive (EMs) or intermediate metabolizers (IMs) of XENAZINE.

Patients who are PMs of XENAZINE will have substantially higher levels of the primary drug metabolites (about 3-fold for α-HTBZ and 9-fold for β-HTBZ) than patients who are EMs. The dosage should be adjusted according to a patient’s CYP2D6 metabolizer status. In patients who are identified as CYP2D6 PMs, the maximum recommended total daily dose is 50 mg and the maximum recommended single dose is 25 mg [see Dosage and Administration (2.2), Use in Specific Populations (8.7), Clinical Pharmacology (12.3)].

5.4 Neuroleptic Malignant Syndrome (NMS)

A potentially fatal symptom complex sometimes referred to as Neuroleptic Malignant Syndrome (NMS) has been reported in association with XENAZINE and other drugs that reduce dopaminergic transmission [see Drug Interactions (7.6)]. Clinical manifestations of NMS are hyperpyrexia, muscle rigidity, altered mental status, and evidence of autonomic instability (irregular pulse or blood pressure, tachycardia, diaphoresis, and cardiac dysrhythmia). Additional signs may include elevated creatinine phosphokinase, myoglobinuria, rhabdomyolysis, and acute renal failure. The diagnosis of NMS can be complicated; other serious medical illness (e.g., pneumonia, systemic infection), and untreated or inadequately treated extrapyramidal disorders can present with similar signs and symptoms. Other important considerations in the differential diagnosis include central anticholinergic toxicity, heat stroke, drug fever, and primary central nervous system pathology.

The management of NMS should include (1) immediate discontinuation of XENAZINE; (2) intensive symptomatic treatment and medical monitoring; and (3) treatment of any concomitant serious medical problems for which specific treatments are available. There is no general agreement about specific pharmacological treatment regimens for NMS.

Recurrence of NMS has been reported with resumption of drug therapy. If treatment with XENAZINE is needed after recovery from NMS, patients should be monitored for signs of recurrence.

5.5 Akathisia, Restlessness, and Agitation

XENAZINE may increase the risk of akathisia, restlessness, and agitation.

In a 12-week, double-blind, placebo-controlled study in patients with chorea associated with HD, akathisia was observed in 10 (19%) of XENAZINE-treated patients and 0% of placebo-treated patients. In an 80-week, open-label study, akathisia was observed in 20% of XENAZINE-treated patients.

Patients receiving XENAZINE should be monitored for the presence of akathisia. Patients receiving XENAZINE should also be monitored for signs and symptoms of restlessness and agitation, as these may be indicators of developing akathisia. If a patient develops akathisia, the XENAZINE dose should be reduced; however, some patients may require discontinuation of therapy.

5.6 Parkinsonism

XENAZINE can cause parkinsonism. In a 12-week, double-blind, placebo-controlled study in patients with chorea associated with HD, symptoms suggestive of parkinsonism (i.e., bradykinesia, hypertonia and rigidity) were observed in 15% of XENAZINE-treated patients compared to 0% of placebo-treated patients. In 48-week and 80-week, open-label studies, symptoms suggestive of parkinsonism were observed in 10% and 3% of XENAZINE-treated patients, respectively.

Because rigidity can develop as part of the underlying disease process in Huntington’s disease, it may be difficult to distinguish between this drug-induced adverse reaction and progression of the underlying disease process. Drug-induced parkinsonism has the potential to cause more functional disability than untreated chorea for some patients with Huntington’s disease. If a patient develops parkinsonism during treatment with XENAZINE, dose reduction should be considered; in some patients, discontinuation of therapy may be necessary.

5.7 Sedation and Somnolence

Sedation is the most common dose-limiting adverse reaction of XENAZINE. In a 12-week, double-blind, placebo-controlled trial in patients with chorea associated with HD, sedation/somnolence occurred in 17/54 (31%) of XENAZINE-treated patients and in 1 (3%) of placebo-treated patient. Sedation was the reason upward titration of XENAZINE was stopped and/or the dose of XENAZINE was decreased in 15/54 (28%) patients. In all but one case, decreasing the dose of XENAZINE resulted in decreased sedation. In 48-week and 80-week, open-label studies, sedation/somnolence occurred in 17% and 57% of XENAZINE-treated patients, respectively. In some patients, sedation occurred at doses that were lower than recommended doses.

Patients should not perform activities requiring mental alertness to maintain the safety of themselves or others, such as operating a motor vehicle or operating hazardous machinery, until they are on a maintenance dose of XENAZINE and know how the drug affects them.

5.8 QTc Prolongation

XENAZINE causes a small increase (about 8 msec) in the corrected QT (QTc) interval. QT prolongation can lead to development of torsade de pointes-type ventricular tachycardia with the risk increasing as the degree of prolongation increases [see Clinical Pharmacology (12.2)]. The use of XENAZINE should be avoided in combination with other drugs that are known to prolong QTc, including antipsychotic medications (e.g., chlorpromazine, haloperidol, thioridazine, ziprasidone), antibiotics (e.g., moxifloxacin), Class 1A (e.g., quinidine, procainamide) and Class III (e.g., amiodarone, sotalol) antiarrhythmic medications or any other medications known to prolong the QTc interval [see Drug Interactions (7.5)].

XENAZINE should also be avoided in patients with congenital long QT syndrome and in patients with a history of cardiac arrhythmias. Certain circumstances may increase the risk of the occurrence of torsade de pointes and/or sudden death in association with the use of drugs that prolong the QTc interval, including (1) bradycardia; (2) hypokalemia or hypomagnesemia; (3) concomitant use of other drugs that prolong the QTc interval; and (4) presence of congenital prolongation of the QT interval [see Clinical Pharmacology (12.2)].

5.9 Hypotension and Orthostatic Hypotension

XENAZINE induced postural dizziness in healthy volunteers receiving single doses of 25 or 50 mg. One subject had syncope, and one subject with postural dizziness had documented orthostasis. Dizziness occurred in 4% of XENAZINE-treated patients (vs. none on placebo) in the 12-week, controlled trial; however, blood pressure was not measured during these events. Monitoring of vital signs on standing should be considered in patients who are vulnerable to hypotension.

5.10 Hyperprolactinemia

XENAZINE elevates serum prolactin concentrations in humans. Following administration of 25 mg to healthy volunteers, peak plasma prolactin levels increased 4- to 5-fold. Tissue culture experiments indicate that approximately one third of human breast cancers are prolactin-dependent in vitro, a factor of potential importance if XENAZINE is being considered for a patient with previously detected breast cancer. Although amenorrhea, galactorrhea, gynecomastia, and impotence can be caused by elevated serum prolactin concentrations, the clinical significance of elevated serum prolactin concentrations for most patients is unknown. Chronic increase in serum prolactin levels (although not evaluated in the XENAZINE development program) has been associated with low levels of estrogen and increased risk of osteoporosis. If there is a clinical suspicion of symptomatic hyperprolactinemia, appropriate laboratory testing should be done and consideration should be given to discontinuation of XENAZINE.

5.11 Binding to Melanin-Containing Tissues

Since XENAZINE or its metabolites bind to melanin-containing tissues, it could accumulate in these tissues over time. This raises the possibility that XENAZINE may cause toxicity in these tissues after extended use. Neither ophthalmologic nor microscopic examination of the eye has been conducted in the chronic toxicity studies in a pigmented species, such as dogs. Ophthalmologic monitoring in humans was inadequate to exclude the possibility of injury occurring after long-term exposure.

The clinical relevance of XENAZINE’s binding to melanin-containing tissues is unknown. Although there are no specific recommendations for periodic ophthalmologic monitoring, prescribers should be aware of the possibility of long-term ophthalmologic effects [see Clinical Pharmacology (12.2)].

6 ADVERSE REACTIONS

The following serious adverse reactions are described below and elsewhere in the labeling:

- Depression and Suicidality [see Warnings and Precautions (5.1)]
- Neuroleptic Malignant Syndrome (NMS) [see Warnings and Precautions (5.4)]
- Akathisia, Restlessness, and Agitation [see Warnings and Precautions (5.5)]
- Parkinsonism [see Warnings and Precautions (5.6)]
- Sedation and Somnolence [see Warnings and Precautions (5.7)]
- QTc Prolongation [see Warnings and Precautions (5.8)]
- Hypotension and Orthostatic Hypotension [see Warnings and Precautions (5.9)]
- Hyperprolactinemia [see Warnings and Precautions (5.10)]
- Binding to Melanin-Containing Tissues [see Warnings and Precautions (5.11)]

6.1 Clinical Trials Experience

Because clinical trials are conducted under widely varying conditions, adverse reaction rates observed in the clinical trials of a drug cannot be directly compared to rates in the clinical trials of another drug and may not reflect the rates observed in practice.

During its development, XENAZINE was administered to 773 unique subjects and patients. The conditions and duration of exposure to XENAZINE varied greatly, and included single-dose and multiple-dose clinical pharmacology studies in healthy volunteers (n=259) and open-label (n=529) and double-blind studies (n=84) in patients.

In a randomized, 12-week, placebo-controlled clinical trial of HD patients, adverse reactions were more common in the XENAZINE group than in the placebo group. Forty-nine of 54 (91%) patients who received XENAZINE experienced one or more adverse reactions at any time during the study. The most common adverse reactions (over 10%, and at least 5% greater than placebo) were sedation/somnolence, fatigue, insomnia, depression, akathisia, anxiety/anxiety aggravated, and nausea.

Adverse Reactions Occurring in Greater Than or Equal to 4% of Patients

The number and percentage of the most common adverse reactions that occurred at any time during the study in greater than or equal to 4% of XENAZINE-treated patients, and with a greater frequency than in placebo-treated patients, are presented in Table 1.

Table 1: Adverse Reactions in a 12-Week, Double-Blind, Placebo-Controlled Trial in Patients with Huntington’s Disease
Adverse Reaction | XENAZINE n=54 % | Placebo n=30 %
Sedation/somnolence | 31 | 3
Insomnia | 22 | 0
Fatigue | 22 | 13
Depression | 19 | 0
Akathisia | 19 | 0
Anxiety/anxiety aggravated | 15 | 3
Fall | 15 | 13
Nausea | 13 | 7
Upper respiratory tract infection | 11 | 7
Irritability | 9 | 3
Balance difficulty | 9 | 0
Parkinsonism/bradykinesia | 9 | 0
Vomiting | 6 | 3
Laceration (head) | 6 | 0
Ecchymosis | 6 | 0
Decreased appetite | 4 | 0
Obsessive reaction | 4 | 0
Dizziness | 4 | 0
Dysarthria | 4 | 0
Unsteady gait | 4 | 0
Headache | 4 | 3
Shortness of breath | 4 | 0
Bronchitis | 4 | 0
Dysuria | 4 | 0

Dose escalation was discontinued or dosage of study drug was reduced because of one or more adverse reactions in 28 of 54 (52%) patients randomized to XENAZINE. These adverse reactions consisted of sedation (15), akathisia (7), parkinsonism (4), depression (3), anxiety (2), fatigue (1) and diarrhea (1). Some patients had more than one AR and are, therefore, counted more than once.

Adverse Reactions Due to Extrapyramidal Symptoms

Table 2 describes the incidence of events considered to be extrapyramidal adverse reactions which occurred at a greater frequency in XENAZINE-treated patients compared to placebo-treated patients.

Table 2: Adverse Reactions Due to Extrapyramidal Symptoms in a 12-Week, Double-Blind, Placebo-Controlled Trial in Patients with Huntington’s Disease
 | XENAZINE n=54 % | Placebo n=30 %
Akathisia [Patients with the following adverse event preferred terms were counted in this category: akathisia, hyperkinesia, restlessness.] | 19 | 0
Extrapyramidal event [Patients with the following adverse event preferred terms were counted in this category: bradykinesia, parkinsonism, extrapyramidal disorder, hypertonia.] | 15 | 0
Any extrapyramidal event | 33 | 0

Patients may have had events in more than one category.

Dysphagia

Dysphagia is a component of HD. However, drugs that reduce dopaminergic transmission have been associated with esophageal dysmotility and dysphagia. Dysphagia may be associated with aspiration pneumonia. In a 12-week, double-blind, placebo-controlled study in patients with chorea associated with HD, dysphagia was observed in 4% of XENAZINE-treated patients and 3% of placebo-treated patients. In 48-week and 80-week, open-label studies, dysphagia was observed in 10% and 8% of XENAZINE-treated patients, respectively. Some of the cases of dysphagia were associated with aspiration pneumonia. Whether these events were related to treatment is unknown.

6.2 Postmarketing Experience

The following adverse reactions have been identified during post-approval use of XENAZINE. Because these reactions are reported voluntarily from a population of uncertain size, it is not always possible to reliably estimate their frequency or establish a causal relationship to drug exposure.

Nervous system disorders: tremor

Psychiatric disorders: confusion, worsening aggression

Respiratory, thoracic and mediastinal disorders: pneumonia

Skin and subcutaneous tissue disorders: hyperhidrosis, skin rash

7 DRUG INTERACTIONS

7.1 Strong CYP2D6 Inhibitors

In vitro studies indicate that α-HTBZ and β-HTBZ are substrates for CYP2D6. Strong CYP2D6 inhibitors (e.g., paroxetine, fluoxetine, quinidine) markedly increase exposure to these metabolites. A reduction in XENAZINE dose may be necessary when adding a strong CYP2D6 inhibitor (e.g., fluoxetine, paroxetine, quinidine) in patients maintained on a stable dose of XENAZINE. The daily dose of XENAZINE should not exceed 50 mg/day and the maximum single dose of XENAZINE should not exceed 25 mg in patients taking strong CYP2D6 inhibitors [see Dosage and Administration (2.3), Warnings and Precautions (5.3), Use in Specific Populations (8.7), Clinical Pharmacology (12.3)].

7.2 Reserpine

Reserpine binds irreversibly to VMAT2, and the duration of its effect is several days. Prescribers should wait for chorea to re-emerge before administering XENAZINE to avoid overdosage and major depletion of serotonin and norepinephrine in the CNS. At least 20 days should elapse after stopping reserpine before starting XENAZINE. XENAZINE and reserpine should not be used concomitantly [see Contraindications (4)].

7.3 Monoamine Oxidase Inhibitors (MAOIs)

XENAZINE is contraindicated in patients taking MAOIs. XENAZINE should not be used in combination with an MAOI, or within a minimum of 14 days of discontinuing therapy with an MAOI [see Contraindications (4)].

7.4 Alcohol or Other Sedating Drugs

Concomitant use of alcohol or other sedating drugs may have additive effects and worsen sedation and somnolence [see Warnings and Precautions (5.7)].

7.5 Drugs That Cause QTc Prolongation

XENAZINE causes a small prolongation of QTc (about 8 msec), concomitant use with other drugs that are known to cause QTc prolongation should be avoided, these including antipsychotic medications (e.g., chlorpromazine, haloperidol, thioridazine, ziprasidone), antibiotics (e.g., moxifloxacin), Class 1A (e.g., quinidine, procainamide) and Class III (e.g., amiodarone, sotalol) antiarrhythmic medications or any other medications known to prolong the QTc interval. XENAZINE should be avoided in patients with congenital long QT syndrome and in patients with a history of cardiac arrhythmias. Certain conditions may increase the risk for torsade de pointes or sudden death such as (1) bradycardia; (2) hypokalemia or hypomagnesemia; (3) concomitant use of other drugs that prolong the QTc interval; and (4) presence of congenital prolongation of the QT interval [see Warnings and Precautions (5.8), Clinical Pharmacology (12.2)].

7.6 Neuroleptic Drugs

The risk for Parkinsonism, NMS, and akathisia may be increased by concomitant use of XENAZINE and dopamine antagonists or antipsychotics (e.g., chlorpromazine, haloperidol, olanzapine, risperidone, thioridazine, ziprasidone) [see Warnings and Precautions (5.4, 5.5, 5.6)].

7.7 Concomitant Deutetrabenazine or Valbenazine

XENAZINE is contraindicated in patients currently taking deutetrabenazine or valbenazine.

8 USE IN SPECIFIC POPULATIONS

8.1 Pregnancy

TERATOGENIC EFFECTS

Risk Summary

There are no adequate data on the developmental risk associated with the use of XENAZINE in pregnant women. Administration of tetrabenazine to rats throughout pregnancy and lactation resulted in an increase in stillbirths and postnatal offspring mortality. Administration of a major human metabolite of tetrabenazine to rats during pregnancy or during pregnancy and lactation produced adverse effects on the developing fetus and offspring (increased mortality, decreased growth, and neurobehavioral and reproductive impairment). The adverse developmental effects of tetrabenazine and a major human metabolite of tetrabenazine in rats occurred at clinically relevant doses [see Data].

In the U.S. general population, the estimated background risk of major birth defects and miscarriage in clinically recognized pregnancies is 2 to 4% and 15 to 20%, respectively. The background risk of major birth defects and miscarriage for the indicated population is unknown.

Data

Animal Data

Tetrabenazine had no clear effects on embryofetal development when administered to pregnant rats throughout the period of organogenesis at oral doses up to 30 mg/kg/day (or 3 times the maximum recommended human dose [MRHD] of 100 mg/day on a mg/m^2 basis). Tetrabenazine had no effects on embryofetal development when administered to pregnant rabbits during the period of organogenesis at oral doses up to 60 mg/kg/day (or 12 times the MRHD on a mg/m^2 basis).

When tetrabenazine (5, 15, and 30 mg/kg/day) was orally administered to pregnant rats from the beginning of organogenesis through the lactation period, an increase in stillbirths and offspring postnatal mortality was observed at 15 and 30 mg/kg/day and delayed pup maturation was observed at all doses. A no-effect dose for pre- and postnatal developmental toxicity in rats was not identified. The lowest dose tested (5 mg/kg/day) was less than the MRHD on a mg/m^2 basis.

Because rats dosed orally with tetrabenazine do not produce 9-desmethyl-β-DHTBZ, a major human metabolite of tetrabenazine, the metabolite was directly administered to pregnant and lactating rats. Oral administration of 9-desmethyl-β-DHTBZ (8, 15, and 40 mg/kg/day) throughout the period of organogenesis produced increases in embryofetal mortality at 15 and 40 mg/kg/day and reductions in fetal body weights at 40 mg/kg/day, which was also maternally toxic. When 9-desmethyl-β-DHTBZ (8, 15, and 40 mg/kg/day) was orally administered to pregnant rats from the beginning of organogenesis through the lactation period, increases in gestation duration, stillbirths, and offspring postnatal mortality (40 mg/kg/day); decreases in pup weights (40 mg/kg/day); and neurobehavioral (increased activity, learning and memory deficits) and reproductive (decreased litter size) impairment (15 and 40 mg/kg/day) were observed. Maternal toxicity was seen at the highest dose. The no-effect dose for developmental toxicity in rats (8 mg/kg/day) was associated with plasma exposures (AUC) of 9-desmethyl-β-DHTBZ in pregnant rats lower than that in humans at the MRHD.

8.2 Lactation

Risk Summary

There are no data on the presence of tetrabenazine or its metabolites in human milk, the effects on the breastfed infant, or the effects of the drug on milk production.

The developmental and health benefits of breastfeeding should be considered along with the mother’s clinical need for XENAZINE and any potential adverse effects on the breastfed infant from XENAZINE or from the underlying maternal condition.

8.4 Pediatric Use

Safety and effectiveness in pediatric patients have not been established.

8.5 Geriatric Use

The pharmacokinetics of XENAZINE and its primary metabolites have not been formally studied in geriatric subjects.

8.6 Hepatic Impairment

Because the safety and efficacy of the increased exposure to XENAZINE and other circulating metabolites are unknown, it is not possible to adjust the dosage of XENAZINE in hepatic impairment to ensure safe use. The use of XENAZINE in patients with hepatic impairment is contraindicated [see Contraindications (4), Clinical Pharmacology (12.3)].

8.7 Poor or Extensive CYP2D6 Metabolizers

Patients who require doses of XENAZINE greater than 50 mg/day, should be first tested and genotyped to determine if they are poor (PMs) or extensive metabolizers (EMs) by their ability to express the drug metabolizing enzyme, CYP2D6. The dose of XENAZINE should then be individualized accordingly to their status as either poor (PMs) or extensive metabolizers (EMs) [see Dosage and Administration (2.2), Warnings and Precautions (5.3), Clinical Pharmacology (12.3)].

Poor Metabolizers

Poor CYP2D6 metabolizers (PMs) will have substantially higher levels of exposure to the primary metabolites (about 3-fold for α-HTBZ and 9-fold for β-HTBZ) compared to EMs. The dosage should, therefore, be adjusted according to a patient’s CYP2D6 metabolizer status by limiting a single dose to a maximum of 25 mg and the recommended daily dose to not exceed a maximum of 50 mg/day in patients who are CYP2D6 PMs [see Dosage and Administration (2.2), Warnings and Precautions (5.3), Clinical Pharmacology (12.3)].

Extensive/Intermediate Metabolizers

In extensive (EMs) or intermediate metabolizers (IMs), the dosage of XENAZINE can be titrated to a maximum single dose of 37.5 mg and a recommended maximum daily dose of 100 mg [see Dosage and Administration (2.2), Drug Interactions (7.1), Clinical Pharmacology (12.3)].

9 DRUG ABUSE AND DEPENDENCE

9.1 Controlled Substance

XENAZINE is not a controlled substance.

9.2 Abuse

Clinical trials did not reveal patients developed drug seeking behaviors, though these observations were not systematic. Abuse has not been reported from the postmarketing experience in countries where XENAZINE has been marketed.

As with any CNS-active drug, prescribers should carefully evaluate patients for a history of drug abuse and follow such patients closely, observing them for signs of XENAZINE misuse or abuse (such as development of tolerance, increasing dose requirements, drug-seeking behavior).

Abrupt discontinuation of XENAZINE from patients did not produce symptoms of withdrawal or a discontinuation syndrome; only symptoms of the original disease were observed to re-emerge [see Dosage and Administration (2.4)].

10 OVERDOSAGE

Three episodes of overdose occurred in the open-label trials performed in support of registration. Eight cases of overdose with XENAZINE have been reported in the literature. The dose of XENAZINE in these patients ranged from 100 mg to 1 g. Adverse reactions associated with XENAZINE overdose include acute dystonia, oculogyric crisis, nausea and vomiting, sweating, sedation, hypotension, confusion, diarrhea, hallucinations, rubor, and tremor.

Treatment should consist of those general measures employed in the management of overdosage with any CNS-active drug. General supportive and symptomatic measures are recommended. Cardiac rhythm and vital signs should be monitored. In managing overdosage, the possibility of multiple drug involvement should always be considered. The physician should consider contacting a poison control center on the treatment of any overdose.

11 DESCRIPTION

XENAZINE (tetrabenazine) is a monoamine depletor for oral administration. The molecular weight of tetrabenazine is 317.43; the pKa is 6.51. Tetrabenazine is a hexahydro-dimethoxy-benzoquinolizine derivative and has the following chemical name: cis rac –1,3,4,6,7,11b-hexahydro-9,10-dimethoxy-3-(2-methylpropyl)-2H-benzo[a]quinolizin-2-one.

The empirical formula C19H27NO3 is represented by the following structural formula:

Tetrabenazine is a white to slightly yellow crystalline powder that is sparingly soluble in water and soluble in ethanol.

Each XENAZINE (tetrabenazine) tablet contains either 12.5 or 25 mg of tetrabenazine as the active ingredient.

XENAZINE (tetrabenazine) tablets contain tetrabenazine as the active ingredient and the following inactive ingredients: lactose, magnesium stearate, maize starch, and talc. The 25 mg strength tablet also contains yellow iron oxide as an inactive ingredient.

XENAZINE (tetrabenazine) tablets are supplied as a yellowish-buff, scored tablet containing 25 mg of tetrabenazine or as a white, non-scored tablet containing 12.5 mg of tetrabenazine.

12 CLINICAL PHARMACOLOGY

12.1 Mechanism of Action

The precise mechanism by which XENAZINE (tetrabenazine) exerts its anti-chorea effects is unknown but is believed to be related to its effect as a reversible depletor of monoamines (such as dopamine, serotonin, norepinephrine, and histamine) from nerve terminals. Tetrabenazine reversibly inhibits the human vesicular monoamine transporter type 2 (VMAT2) (Ki ≈ 100 nM), resulting in decreased uptake of monoamines into synaptic vesicles and depletion of monoamine stores. Human VMAT2 is also inhibited by dihydrotetrabenazine (HTBZ), a mixture of α-HTBZ and β-HTBZ. α- and β-HTBZ, major circulating metabolites in humans, exhibit high in vitro binding affinity to bovine VMAT2. Tetrabenazine exhibits weak in vitro binding affinity at the dopamine D2 receptor (Ki = 2100 nM).

12.2 Pharmacodynamics

QTc Prolongation

The effect of a single 25 or 50 mg dose of XENAZINE on the QT interval was studied in a randomized, double-blind, placebo-controlled crossover study in healthy male and female subjects with moxifloxacin as a positive control. At 50 mg, XENAZINE caused an approximately 8 msec mean increase in QTc (90% CI: 5.0, 10.4 msec). Additional data suggest that inhibition of CYP2D6 in healthy subjects given a single 50 mg dose of XENAZINE does not further increase the effect on the QTc interval. Effects at higher exposures to either XENAZINE or its metabolites have not been evaluated [see Warnings and Precautions (5.8), Drug Interactions (7.5)].

Melanin Binding

Tetrabenazine or its metabolites bind to melanin-containing tissues (i.e., eye, skin, fur) in pigmented rats. After a single oral dose of radiolabeled tetrabenazine, radioactivity was still detected in eye and fur at 21 days post dosing [see Warnings and Precautions (5.11)].

12.3 Pharmacokinetics

Absorption

Following oral administration of tetrabenazine, the extent of absorption is at least 75%. After single oral doses ranging from 12.5 to 50 mg, plasma concentrations of tetrabenazine are generally below the limit of detection because of the rapid and extensive hepatic metabolism of tetrabenazine by carbonyl reductase to the active metabolites α-HTBZ and β-HTBZ. α-HTBZ and β-HTBZ are metabolized principally by CYP2D6. Peak plasma concentrations (Cmax) of α-HTBZ and β-HTBZ are reached within 1 to 1½ hours post-dosing. α-HTBZ is subsequently metabolized to a minor metabolite, 9-desmethyl-α-DHTBZ. β-HTBZ is subsequently metabolized to another major circulating metabolite, 9-desmethyl-β-DHTBZ, for which Cmax is reached approximately 2 hours post-dosing.

Food Effects

The effects of food on the bioavailability of XENAZINE were studied in subjects administered a single dose with and without food. Food had no effect on mean plasma concentrations, Cmax, or the area under the concentration time course (AUC) of α-HTBZ or β-HTBZ [see Dosage and Administration (2.1)].

Distribution

Results of PET-scan studies in humans show that radioactivity is rapidly distributed to the brain following intravenous injection of ^11C-labeled tetrabenazine or α-HTBZ, with the highest binding in the striatum and lowest binding in the cortex.

The in vitro protein binding of tetrabenazine, α-HTBZ, and β-HTBZ was examined in human plasma for concentrations ranging from 50 to 200 ng/mL. Tetrabenazine binding ranged from 82% to 85%, α-HTBZ binding ranged from 60% to 68%, and β-HTBZ binding ranged from 59% to 63%.

Metabolism

After oral administration in humans, at least 19 metabolites of tetrabenazine have been identified. α-HTBZ, β-HTBZ and 9-desmethyl-β-DHTBZ are the major circulating metabolites and are subsequently metabolized to sulfate or glucuronide conjugates. α-HTBZ and β-HTBZ are formed by carbonyl reductase that occurs mainly in the liver. α-HTBZ is O-dealkylated by CYP450 enzymes, principally CYP2D6, with some contribution of CYP1A2 to form 9-desmethyl-α-DHTBZ, a minor metabolite. β-HTBZ is O-dealkylated principally by CYP2D6 to form 9-desmethyl-β-DHTBZ.

The results of in vitro studies do not suggest that tetrabenazine, α-HTBZ, β-HTBZ or 9-desmethyl-β-DHTBZ are likely to result in clinically significant inhibition of CYP2D6, CYP1A2, CYP2B6, CYP2C8, CYP2C9, CYP2C19, CYP2E1, or CYP3A. In vitro studies suggest that neither tetrabenazine nor its α- or β-HTBZ or 9-desmethyl-β-DHTBZ metabolites are likely to result in clinically significant induction of CYP1A2, CYP3A4, CYP2B6, CYP2C8, CYP2C9, or CYP2C19.

Neither tetrabenazine nor its α- or β-HTBZ or 9-desmethyl-β-DHTBZ metabolites are likely to be substrates or inhibitors of P-glycoprotein at clinically relevant concentrations in vivo.

Elimination

After oral administration, tetrabenazine is extensively hepatically metabolized, and the metabolites are primarily renally eliminated. α-HTBZ, β-HTBZ and 9-desmethyl-β-DHTBZ have half-lives of 7 hours, 5 hours and 12 hours respectively. In a mass balance study in 6 healthy volunteers, approximately 75% of the dose was excreted in the urine, and fecal recovery accounted for approximately 7 to 16% of the dose. Unchanged tetrabenazine has not been found in human urine. Urinary excretion of α-HTBZ or β-HTBZ accounted for less than 10% of the administered dose. Circulating metabolites, including sulfate and glucuronide conjugates of HTBZ metabolites as well as products of oxidative metabolism, account for the majority of metabolites in the urine.

Specific Populations

Gender

There is no apparent effect of gender on the pharmacokinetics of α-HTBZ or β-HTBZ.

Hepatic Impairment

The disposition of tetrabenazine was compared in 12 patients with mild to moderate chronic liver impairment (Child-Pugh scores of 5-9) and 12 age- and gender-matched subjects with normal hepatic function who received a single 25 mg dose of tetrabenazine. In patients with hepatic impairment, tetrabenazine plasma concentrations were similar to or higher than concentrations of α-HTBZ, reflecting the markedly decreased metabolism of tetrabenazine to α-HTBZ. The mean tetrabenazine Cmax in subjects with hepatic impairment was approximately 7- to 190-fold higher than the detectable peak concentrations in healthy subjects. The elimination half-life of tetrabenazine in subjects with hepatic impairment was approximately 17.5 hours. The time to peak concentrations (tmax) of α-HTBZ and β-HTBZ was slightly delayed in subjects with hepatic impairment compared to age-matched controls (1.75 hrs vs. 1.0 hrs), and the elimination half-lives of the α-HTBZ and β-HTBZ were prolonged to approximately 10 and 8 hours, respectively. The exposure to α-HTBZ and β-HTBZ was approximately 30% to 39% greater in patients with liver impairment than in age-matched controls. The safety and efficacy of this increased exposure to tetrabenazine and other circulating metabolites are unknown so that it is not possible to adjust the dosage of tetrabenazine in hepatic impairment to ensure safe use. Therefore, XENAZINE is contraindicated in patients with hepatic impairment [see Contraindications (4), Use in Specific Populations (8.6)].

Poor CYP2D6 Metabolizers

Although the pharmacokinetics of XENAZINE and its metabolites in patients who do not express the drug metabolizing enzyme, CYP2D6, poor metabolizers, (PMs), have not been systematically evaluated, it is likely that the exposure to α-HTBZ and β-HTBZ would be increased similar to that observed in patients taking strong CYP2D6 inhibitors (3- and 9-fold, respectively) [see Dosage and Administration (2.3), Warnings and Precautions (5.3), Use in Specific Populations (8.7)].

Drug Interactions

CYP2D6 Inhibitors

In vitro studies indicate that α-HTBZ and β-HTBZ are substrates for CYP2D6. The effect of CYP2D6 inhibition on the pharmacokinetics of tetrabenazine and its metabolites was studied in 25 healthy subjects following a single 50 mg dose of tetrabenazine given after 10 days of administration of the strong CYP2D6 inhibitor paroxetine 20 mg daily. There was an approximately 30% increase in Cmax and an approximately 3-fold increase in AUC for α-HTBZ in subjects given paroxetine prior to tetrabenazine compared to tetrabenazine given alone. For β-HTBZ, the Cmax and AUC were increased 2.4- and 9-fold, respectively, in subjects given paroxetine prior to tetrabenazine given alone. The elimination half-life of α-HTBZ and β-HTBZ was approximately 14 hours when tetrabenazine was given with paroxetine.

Strong CYP2D6 inhibitors (e.g., paroxetine, fluoxetine, quinidine) markedly increase exposure to these metabolites. The effect of moderate or weak CYP2D6 inhibitors such as duloxetine, terbinafine, amiodarone, or sertraline on the exposure to XENAZINE and its metabolites has not been evaluated [see Dosage and Administration (2.3), Warnings and Precautions (5.3), Drug Interactions (7.1), Use in Specific Populations (8.7)].

Digoxin

Digoxin is a substrate for P-glycoprotein. A study in healthy volunteers showed that XENAZINE (25 mg twice daily for 3 days) did not affect the bioavailability of digoxin, suggesting that at this dose, XENAZINE does not affect P-glycoprotein in the intestinal tract. In vitro studies also do not suggest that XENAZINE or its metabolites are P-glycoprotein inhibitors.

13 NONCLINICAL TOXICOLOGY

13.1 Carcinogenesis, Mutagenesis, Impairment of Fertility

Carcinogenesis

No increase in tumors was observed in p53+/- transgenic mice treated orally with tetrabenazine (5, 15, and 30 mg/kg/day) for 26 weeks.

No increase in tumors was observed in Tg.rasH2 transgenic mice treated orally with a major human metabolite, 9-desmethyl-β-DHTBZ (20, 100, and 200 mg/kg/day), for 26 weeks.

Mutagenesis

Tetrabenazine and metabolites α-HTBZ, β-HTBZ, and 9-desmethyl-β-DHTBZ were negative in an in vitro bacterial reverse mutation assay. Tetrabenazine was clastogenic in an in vitro chromosomal aberration assay in Chinese hamster ovary cells in the presence of metabolic activation. α-HTBZ and β-HTBZ were clastogenic in an in vitro chromosome aberration assay in Chinese hamster lung cells in the presence and absence of metabolic activation. 9-desmethyl-β-DHTBZ was not clastogenic in an in vitro chromosomal aberration assay in human peripheral blood mononuclear cells in the presence or absence of metabolic activation. In vivo micronucleus assays were conducted in male and female rats and male mice. Tetrabenazine was negative in male mice and rats but produced an equivocal response in female rats.

Impairment of Fertility

Oral administration of tetrabenazine (5, 15, or 30 mg/kg/day) to female rats prior to and throughout mating, and continuing through day 7 of gestation resulted in disrupted estrous cyclicity at doses greater than 5 mg/kg/day (less than the MRHD on a mg/m^2 basis).

No effects on mating and fertility indices or sperm parameters (motility, count, density) were observed when males were treated orally with tetrabenazine (5, 15, or 30 mg/kg/day; up to 3 times the MRHD on a mg/m^2 basis) prior to and throughout mating with untreated females.

Because rats dosed with tetrabenazine do not produce 9-desmethyl-β-DHTBZ, a major human metabolite, these studies may not have adequately assessed the potential of XENAZINE to impair fertility in humans.

14 CLINICAL STUDIES

Study 1

The efficacy of XENAZINE as a treatment for the chorea of Huntington’s disease was established primarily in a randomized, double-blind, placebo-controlled multi-center trial (Study 1) conducted in ambulatory patients with a diagnosis of HD. The diagnosis of HD was based on family history, neurological exam, and genetic testing. Treatment duration was 12 weeks, including a 7-week dose titration period and a 5-week maintenance period followed by a 1-week washout. XENAZINE was started at a dose of 12.5 mg/day, followed by upward titration at weekly intervals, in 12.5 mg increments until satisfactory control of chorea was achieved, intolerable side effects occurred, or until a maximal dose of 100 mg/day was reached.

The primary efficacy endpoint was the Total Chorea Score, an item of the Unified Huntington’s Disease Rating Scale (UHDRS). On this scale, chorea is rated from 0 to 4 (with 0 representing no chorea) for 7 different parts of the body. The total score ranges from 0 to 28.

As shown in Figure 1, Total Chorea Scores for patients in the drug group declined by an estimated 5.0 units during maintenance therapy (average of Week 9 and Week 12 scores versus baseline), compared to an estimated 1.5 units in the placebo group. The treatment effect of 3.5 units was statistically significant. At the Week 13 follow-up in Study 1 (1 week after discontinuation of the study medication), the Total Chorea Scores of patients receiving XENAZINE returned to baseline.

Figure 1: Mean ± s.e.m. Changes from Baseline in Total Chorea Score in 84 HD Patients Treated with XENAZINE (n=54) or Placebo (n=30)

Figure 2 illustrates the cumulative percentages of patients from the XENAZINE and placebo treatment groups who achieved the level of reduction in the Total Chorea Score shown on the X axis. The left-ward shift of the curve (toward greater improvement) for the XENAZINE-treated patients indicates that these patients were more likely to have any given degree of improvement in chorea score. For example, about 7% of placebo patients had a 6-point or greater improvement compared to 50% of XENAZINE-treated patients. The percentage of patients achieving reductions of at least 10, 6, and 3 points from baseline to Week 12 are shown in the inset table.

Figure 2: Cumulative Percentage of Patients with Specified Changes from Baseline in Total Chorea Score. The Percentages of Randomized Patients Within Each Treatment Group Who Completed Study 1 Were: Placebo 97%, Tetrabenazine 91%

A Physician-rated Clinical Global Impression (CGI) favored XENAZINE statistically. In general, measures of functional capacity and cognition showed no difference between XENAZINE and placebo. However, one functional measure (Part 4 of the UHDRS), a 25-item scale assessing the capacity for patients to perform certain activities of daily living, showed a decrement for patients treated with XENAZINE compared to placebo, a difference that was nominally statistically significant. A 3-item cognitive battery specifically developed to assess cognitive function in patients with HD (Part 2 of the UHDRS) also showed a decrement for patients treated with XENAZINE compared to placebo, but the difference was not statistically significant.

Study 2

A second controlled study was performed in patients who had been treated with open-label XENAZINE for at least 2 months (mean duration of treatment was 2 years). They were randomized to continuation of XENAZINE at the same dose (n=12) or to placebo (n=6) for three days, at which time their chorea scores were compared. Although the comparison did not reach statistical significance (p=0.1), the estimate of the treatment effect was similar to that seen in Study 1 (about 3.5 units).

16 HOW SUPPLIED/STORAGE AND HANDLING

16.1 How Supplied

XENAZINE® (tetrabenazine) tablets are available in the following strengths and packages:

The 12.5 mg XENAZINE tablets are white, cylindrical, biplanar tablets with beveled edges, non-scored, embossed on one side with “CL” and “12.5”.

- NDC 67386-421-01 12.5 mg 112-count bottle

The 25 mg XENAZINE tablets are yellowish-buff, cylindrical, biplanar tablets with beveled edges, scored, embossed on one side with “CL” and “25”.

- NDC 67386-422-01 25 mg 112-count bottle

16.2 Storage

Store at 25°C (77°F); excursions permitted to 15° to 30°C (59° to 86°F) [see USP Controlled Room Temperature].

17 PATIENT COUNSELING INFORMATION

Advise the patient to read the FDA-approved patient labeling (Medication Guide).

Risk of Suicidality

Inform patients and their families that XENAZINE may increase the risk of suicidal thinking and behaviors. Counsel patients and their families to remain alert to the emergence of suicidal ideation and to report it immediately to the patient’s physician [see Contraindications (4), Warnings and Precautions (5.1)].

Risk of Depression

Inform patients and their families that XENAZINE may cause depression or may worsen pre-existing depression. Encourage patients and their families to be alert to the emergence of sadness, worsening of depression, withdrawal, insomnia, irritability, hostility (aggressiveness), akathisia (psychomotor restlessness), anxiety, agitation, or panic attacks and to report such symptoms promptly to the patient’s physician [see Contraindications (4), Warnings and Precautions (5.1)].

Dosing of XENAZINE

Inform patients and their families that the dose of XENAZINE will be increased slowly to the dose that is best for each patient. Sedation, akathisia, parkinsonism, depression, and difficulty swallowing may occur. Such symptoms should be promptly reported to the physician, and the XENAZINE dose may need to be reduced or discontinued [see Dosage and Administration (2.2)].

Risk of Sedation and Somnolence

Inform patients that XENAZINE may induce sedation and somnolence and may impair the ability to perform tasks that require complex motor and mental skills. Advise patients that until they learn how they respond to XENAZINE, they should be careful doing activities that require them to be alert, such as driving a car or operating machinery [see Warnings and Precautions (5.7)].

Interaction with Alcohol

Advise patients and their families that alcohol may potentiate the sedation induced by XENAZINE [see Drug Interactions (7.4)].

Usage in Pregnancy

Advise patients and their families to notify the physician if the patient becomes pregnant or intends to become pregnant during XENAZINE therapy, or is breastfeeding or intending to breastfeed an infant during therapy [see Use in Specific Populations (8.1)].

Manufactured by:
Recipharm Fontaine SAS
Rue des Prés Potets
21121 Fontaine-lés-Dijon, France

Manufactured for:
Lundbeck
Deerfield, IL 60015 USA

Xenazine is a trademark of Bausch Health Companies Inc. or its affiliates.

All other product/brand names and/or logos are trademarks of the respective owners.

© 2020 Bausch Health Companies Inc. or its affiliates

9465504

MEDICATION GUIDE

XENAZINE® (ZEN-uh-zeen)
(tetrabenazine) Tablets

Read the Medication Guide that comes with XENAZINE before you start taking it and each time you refill the prescription. There may be new information. This information does not take the place of talking with your doctor about your medical condition or your treatment. You should share this information with your family members and caregivers.

What is the most important information I should know about XENAZINE?

- XENAZINE can cause serious side effects, including:
  - depression
  - suicidal thoughts
  - suicidal actions
- You should not start taking XENAZINE if you are depressed (have untreated depression or depression that is not well controlled by medicine) or have suicidal thoughts.
- Pay close attention to any changes, especially sudden changes, in mood, behaviors, thoughts or feelings. This is especially important when XENAZINE is started and when the dose is changed.

Call the doctor right away if you become depressed or have any of the following symptoms, especially if they are new, worse, or worry you:

- feel sad or have crying spells
- lose interest in seeing your friends or doing things you used to enjoy
- sleep a lot more or a lot less than usual
- feel unimportant
- feel guilty
- feel hopeless or helpless
- more irritable, angry or aggressive than usual
- more or less hungry than usual or notice a big change in your body weight
- have trouble paying attention
- feel tired or sleepy all the time
- have thoughts about hurting yourself or ending your life

What is XENAZINE?

XENAZINE is a medicine that is used to treat the involuntary movements (chorea) of Huntington’s disease. XENAZINE does not cure the cause of the involuntary movements, and it does not treat other symptoms of Huntington’s disease, such as problems with thinking or emotions.

It is not known whether XENAZINE is safe and effective in children.

Who should not take XENAZINE?

Do not take XENAZINE if you:

- are depressed or have thoughts of suicide. See “What is the most important information I should know about XENAZINE?”
- have liver problems.
- are taking a monoamine oxidase inhibitor (MAOI) medicine. Ask your doctor or pharmacist if you are not sure.
- are taking reserpine. Do not take medicines that contain reserpine (such as Serpalan and Renese-R) with XENAZINE. If your doctor plans to switch you from taking reserpine to XENAZINE, you must wait at least 20 days after your last dose of reserpine before you start taking XENAZINE.

What should I tell my doctor before taking XENAZINE?

Tell your doctor about all your medical conditions, including if you:

- have emotional or mental problems (for example, depression, nervousness, anxiety, anger, agitation, psychosis, previous suicidal thoughts or suicide attempts).
- have liver disease.
- have any allergies. See the end of this Medication Guide for a complete list of the ingredients in XENAZINE.
- have breast cancer or a history of breast cancer.
- have heart disease that is not stable, have heart failure or recently had a heart attack.
- have an irregular heartbeat (cardiac arrhythmia).
- are pregnant or plan to become pregnant. It is not known if XENAZINE can harm your unborn baby.
- are breastfeeding. It is not known if XENAZINE passes into breast milk.

Tell your doctor about all the medicines you take, including prescription medicines and nonprescription medicines, vitamins and herbal products. Using XENAZINE with certain other medicines may cause serious side effects. Do not start any new medicines while taking XENAZINE without talking to your doctor first.

How should I take XENAZINE?

- XENAZINE is a tablet that you take by mouth.
- Take XENAZINE exactly as prescribed by your doctor.
- You may take XENAZINE with or without food.
- Your doctor will increase your dose of XENAZINE each week for several weeks, until you and your doctor find the best dose for you.
- If you stop taking XENAZINE or miss a dose, your involuntary movements may return or worsen in 12 to 18 hours after the last dose.
- Before starting XENAZINE, you should talk to your healthcare provider about what to do if you miss a dose. If you miss a dose and it is time for your next dose, do not double the dose.
- Tell your doctor if you stop taking XENAZINE for more than 5 days. Do not take another dose until you talk to your doctor.
- If your doctor thinks you need to take more than 50 mg of XENAZINE each day, you will need to have a blood test to see if it is safe for you.

What should I avoid while taking XENAZINE?

Sleepiness (sedation) is a common side effect of XENAZINE. While taking XENAZINE, do not drive a car or operate dangerous machinery until you know how XENAZINE affects you. Drinking alcohol and taking other drugs that may also cause sleepiness while you are taking XENAZINE may increase any sleepiness caused by XENAZINE.

What are the possible side effects of XENAZINE?

XENAZINE can cause serious side effects, including:

- Depression, suicidal thoughts, or actions. See "What is the most important information I should know about XENAZINE?"
- Neuroleptic Malignant Syndrome (NMS). Call your doctor right away and go to the nearest emergency room if you develop these signs and symptoms that do not have another obvious cause:
  - high fever
  - stiff muscles
  - problems thinking
  - very fast or uneven heartbeat
  - increased sweating
- Parkinsonism. Symptoms of Parkinsonism include: slight shaking, body stiffness, trouble moving or keeping your balance.
- Restlessness. You may get a condition where you feel a strong urge to move. This is called akathisia.
- Irregular heartbeat. XENAZINE increases your chance of having certain changes in the electrical activity in your heart which can be seen on an electrocardiogram (EKG). These changes can lead to a dangerous abnormal heartbeat. Taking XENAZINE with certain medicines may increase this chance.
- Dizziness due to blood pressure changes when you change position (orthostatic hypotension). Change positions slowly from lying down to sitting up and from sitting up to standing when taking XENAZINE. Tell your doctor right away if you get dizzy or faint while taking XENAZINE. Your doctor may need to watch your blood pressure closely.

Common side effects with XENAZINE include:

- sleepiness (sedation)
- trouble sleeping
- depression
- tiredness (fatigue)
- anxiety
- restlessness
- agitation
- nausea

Tell your doctor if you have any side effects. Do not stop taking XENAZINE without talking to your doctor first.

Call your doctor for medical advice about side effects. You may report side effects to the Food and Drug Administration (FDA) at 1-800-FDA-1088.

General information about XENAZINE

XENAZINE contains the active ingredient tetrabenazine. It also contains these inactive ingredients: lactose, maize starch, talc, and magnesium stearate. The 25 mg tablet, which is pale yellow, also contains yellow iron oxide.

Medicines are sometimes prescribed for purposes other than those listed in a Medication Guide. Do not use XENAZINE for a condition for which it was not prescribed. Do not give XENAZINE to other people, even if they have the same symptoms that you have. It may harm them. Keep XENAZINE out of the reach of children.

This Medication Guide summarizes the most important information about XENAZINE. If you would like more information, talk with your doctor. You can ask your doctor or pharmacist for information about XENAZINE that is written for healthcare professionals. You can also call Lundbeck’s XENAZINE Information Center at 1-888-882-6013 (option 1) or visit www.xenazineusa.com.

This Medication Guide has been approved by the U.S. Food and Drug Administration.

Manufactured by:
Recipharm Fontaine SAS
Rue des Prés Potets
21121 Fontaine-lés-Dijon, France

Manufactured for:
Lundbeck
Deerfield, IL 60015 USA

Xenazine is a trademark of Bausch Health Companies Inc. or its affiliates.

All other product/brand names and/or logos are trademarks of the respective owners.

© 2020 Bausch Health Companies Inc. or its affiliates

Revised 11/2019

9465504

PACKAGE LABEL

PRINCIPAL DISPLAY PANEL - 12.5 mg Carton

NDC 67386-421-01
112 Tablets
Xenazine®
(tetrabenazine) Tablets

12.5 mg

PHARMACIST: Dispense the
accompanying Medication Guide
to each patient.
GO TO www.xenazineusa.com
Rx only

PACKAGE LABEL

PRINCIPAL DISPLAY PANEL - 25 mg Carton

NDC 67386-422-01
112 Tablets
Xenazine®
(tetrabenazine) Tablets

25 mg

PHARMACIST: Dispense the
accompanying Medication Guide
to each patient.
GO TO www.xenazineusa.com
Rx only